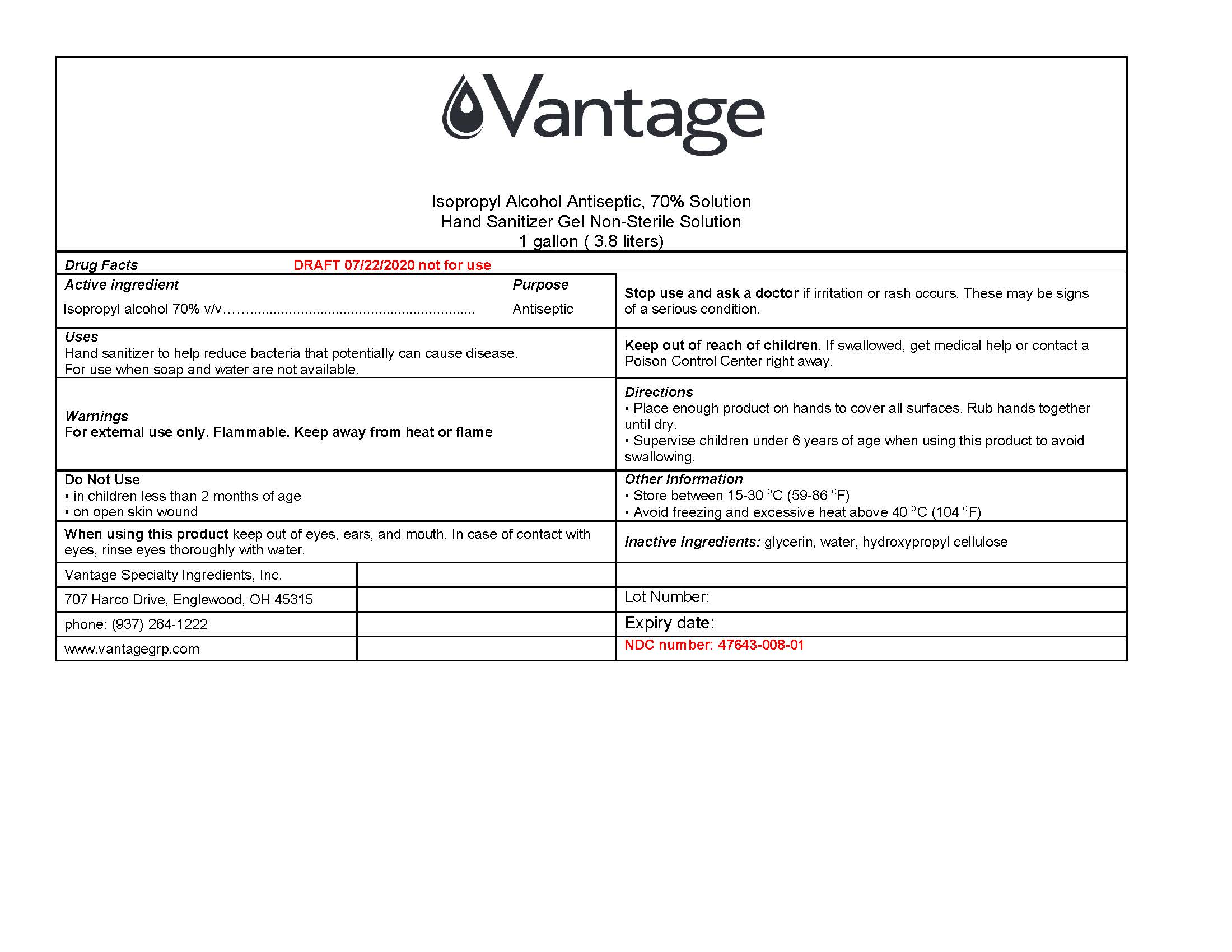 DRUG LABEL: Vanitizer I-200
NDC: 47643-008 | Form: GEL
Manufacturer: Vantage Specialties Ingredients, Inc
Category: otc | Type: HUMAN OTC DRUG LABEL
Date: 20201016

ACTIVE INGREDIENTS: ISOPROPYL ALCOHOL 70 mL/100 mL
INACTIVE INGREDIENTS: WATER; GLYCERIN; HYDROXYPROPYL CELLULOSE (TYPE M)

Vanitizer I-200

Active Ingredient(s)

Isopropyl Alcohol 70% v/v. Purpose: Antiseptic

Uses

Hand Sanitizer to help reduce bacteria that potentially can cause disease. For use when soap and water are not available.

Warnings

For external use only.

Flammable. Keep away from heat or flame.

When using this product keep out of eyes, ears and mouth. In case of contact, rinse eyes thoroughly with water.

Stop use and ask a doctor if irritation or rash occurs. These may be signs of a serious condition.

Keep out of reach of children. If swallowed, get medical help or contact a Poison Control Center right away.

Do Not Use

in children less than 2 months of age

on open skin wounds

Directions

Place enough product on hands to cover all surfaces. Rub hands together until dry.
Supervise children under 6 years of age when using this product to avoid swallowing.

Other Information

Store between 15-30C (59-86F)
Avoid freezing and excessive heat above 40C (104F)

Inactive Ingredients

glycerin, purified water USP, hydroxypropyl cellulose

Keep out of reach of Childern

If swallowed, get medical help or contact a Poison Control Center right away.